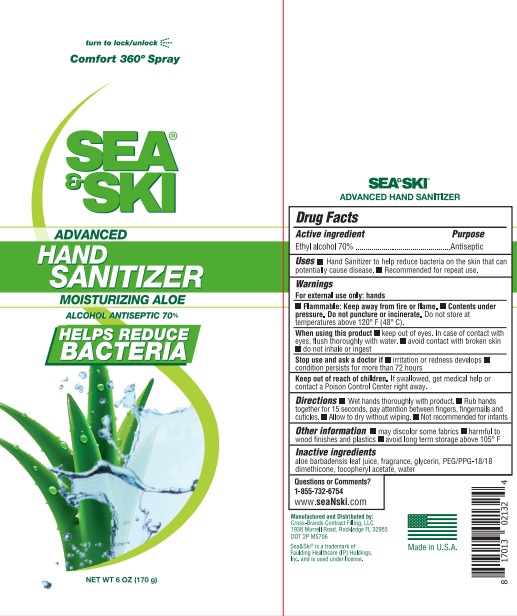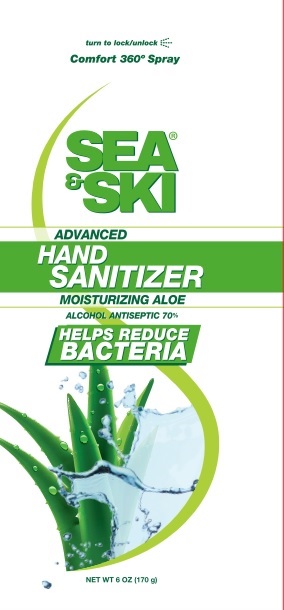 DRUG LABEL: Sea and Ski Hand Sanitizer
NDC: 73440-2132 | Form: SPRAY
Manufacturer: Cross-Brands Contract Filling
Category: otc | Type: HUMAN OTC DRUG LABEL
Date: 20210219

ACTIVE INGREDIENTS: ALCOHOL 119 g/170 g
INACTIVE INGREDIENTS: WATER

Sea & Ski Advanced Hand Sanitizer Spray

Active ingredient

Ethyl Alcohol 70%

Purpose

Antiseptic

Uses

Hand Sanitizer to help reduce baceria on the skin that can potentially cause disease. Recommended for repeat use.

Warnings

For external use only: hands

When Using

When using this product keep out of eyes. In case of contact with eyes, flush thoroughly with water. avoid contact with broken skin do not inhale or ingest

Stop Use

Stop use and ask a doctor if irritation or redness develops condition persists for more than 72 hours

Keep out of reach of children. If swallowed, get medical help or contact a Poison Control Center right away.

Flammable

Flammable:Keep away from fire or flame. Contents under pressure. Do not puncture or incinerate. D not store at temperatures above 120° F (48° C).

Directions

Wet hands thoroughly with product. Rub hands together for 15 seconds, pay attention between fingers, fingernails and cuticles. Allow to dry without wiping. Not recommended for infants

Other Information

may discolor some fabrics harmful to wood finishes and plastics avoid long term storage above 105° F

Inactive ingredients

aloe barbadensis leaf juice, fragrance, glycerin, PEG/PPG-18/18 dimethicone, tocopheryl acetate, water